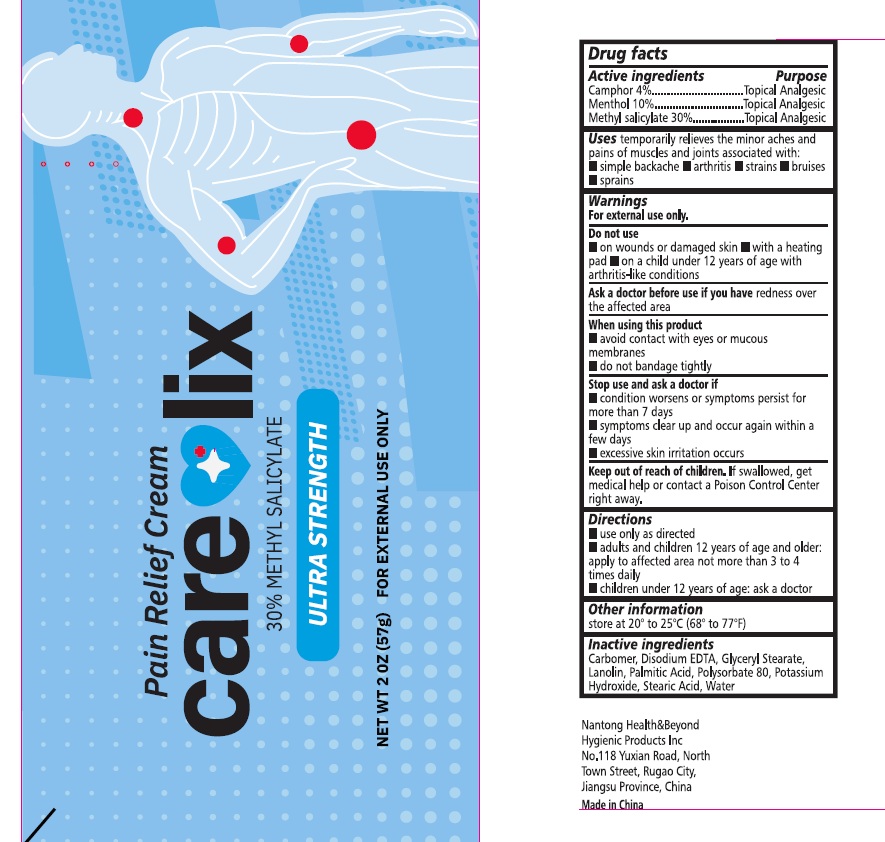 DRUG LABEL: Care Lix Pain Relief
NDC: 87371-001 | Form: CREAM
Manufacturer: ACQUIRED B SCALE LLC
Category: otc | Type: HUMAN OTC DRUG LABEL
Date: 20260205

ACTIVE INGREDIENTS: CAMPHOR (NATURAL) 4 g/100 g; MENTHOL 10 g/100 g; METHYL SALICYLATE 30 g/100 g
INACTIVE INGREDIENTS: WATER; CARBOMER; DISODIUM HEDTA; LANOLIN; POTASSIUM HYDROXIDE; GLYCERYL STEARATE; PALMITIC ACID; POLYSORBATE 80; STEARIC ACID

87371-001 SALICYLIC ACID Pain Relief Cream

Active ingredient

Camphor 4%

Menthol 10%

Methyl Salicylate 30%

Purpose

Topical Analgesic

Topical Analgesic

Topical Analgesic

Uses

Temporarily relieves the minor aches and pains of muscles and joints associated with:

- simple backaches
- arthritis
- strains
- bruises
- sprains

Warnings

For external use only.

Do not use

on wounds or damaged skin

with a heating pad

on a child under 12 years of age with arthritis like conditions

Ask a doctor before use if you haveredness over the affected area

When using this product

- avoid contact with eyes or mucous membranes
- do not bandage tightly

Stop use and ask a doctor if

- condition worsens or symptoms persist for more than 7 days
- symptoms clear up and worsen again within a few days
- excessive skin ittitation occurs

Keep out of reach of children. If swallowed, get medical help or contact a Poison Control Center right away

Directions

- use only as directed
- adult and children 12 years of age and older: apply to affected area not more than 3-4 times daily
- children under 12 years of age: ask a doctor

Other information

Store at 20 to 25 C (60 to 77F)

Inactive ingredients

Carbomer, Disodium EDTA, Glyceryl Stearate, Lanolin, Palmitic Acid, Polysorbate 80, Potassium Hydroxide, Stearic Acid, Water